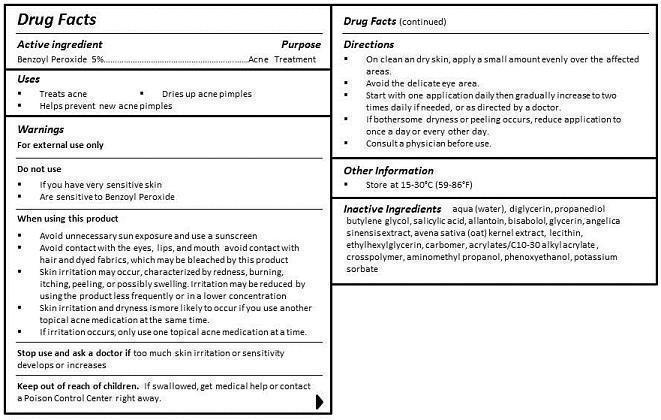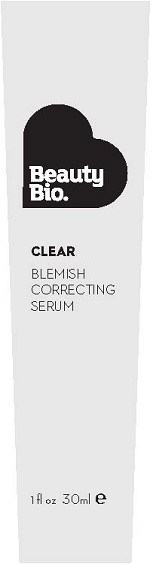 DRUG LABEL: BLEMISH CORRECTING SERUM
NDC: 54272-102 | Form: GEL
Manufacturer: CEN BEAUTY LLC
Category: otc | Type: HUMAN OTC DRUG LABEL
Date: 20130226

ACTIVE INGREDIENTS: BENZOYL PEROXIDE 5 g/100 mL
INACTIVE INGREDIENTS: WATER; DIGLYCERIN; PROPANEDIOL; BUTYLENE GLYCOL; SALICYLIC ACID; ALLANTOIN; .ALPHA.-BISABOLOL, (+/-)-; GLYCERIN; ANGELICA SINENSIS WHOLE; GLYCERIN; ANGELICA SINENSIS WHOLE; AVENA SATIVA TOP; LECITHIN, SOYBEAN; ETHYLHEXYLGLYCERIN; CARBOMER 934; CARBOMER COPOLYMER TYPE A (ALLYL PENTAERYTHRITOL CROSSLINKED); AMINOMETHYLPROPANOL; PHENOXYETHANOL; POTASSIUM SORBATE

ACTIVE INGREDIENT

BENZOYL PEROXIDE 5%

PURPOSE

ACNE TREATMENT

USES

- TREATS ACNE
- DRIES UP ACNE PIMPLES
- HELPS PREVENT NEW ACNE PIMPLES

WARNINGS

FOR EXTERNAL USE ONLY

DO NOT USE

- IF YOU HAVE VERY SENSITIVE SKIN
- ARE SENSITIVE TO BENZOYL PEROXIDE

WHEN USING THIS PRODUCT

- AVOID UNNECESSARY SUN EXPOSURE AND USE A SUNSCREEN
- AVOID CONTACT WITH THE EYES, LIPS, AND MOUTH. AVOID CONTACT WITH HAIR AND DYED FABRICS, WHICH MAY BE BLEACHED BY THE PRODUCT.
- SKIN IRRITATION MAY OCCUR, CHARACTERIZED BY REDNESS, BURNING, ITCHING, PEELING, OR POSSIBLY SWELLING. IRRITATION MAY BE REDUCED BY USING THE PRODUCT LESS FREQUENTLY OR IN A LOWER CONCENTRATION.
- SKIN IRRITATION AND DRYNESS IS MORE LIKELY TO OCCUR IF YOU USE ANOTHER TOPICAL ACNE MEDICATION AT THE SAME TIME.
- IF IRRITATION OCCURS, ONLY USE ONE TOPICAL ACNE MEDICATION AT A TIME.

STOP USE AND ASK A DOCTOR IF TOO MUCH SKIN IRRITATION OR SENSITIVITY DEVELOPS OR INCREASES.

KEEP OUT OF REACH OF CHILDREN. IF SWALLOWED, GET MEDICAL HELP OR CONTACT A POISON CONTROL CENTER RIGHT AWAY.

DIRECTIONS

- ON CLEAN AND DRY SKIN, APPLY A SMALL AMOUNT EVENLY OVER THE AFFECTED AREAS.
- AVOID THE DELICATE EYE AREA.
- START WITH ONE APPLICATION DAILY THEN GRADUALLY INCREASE TO TWO TIMES DAILY IF NEEDED, OR AS DIRECTED BY A DOCTOR.
- IF BOTHERSOME DRYNESS OR PEELING OCCURS, REDUCE APPLICATION TO ONCE A DAY OR EVERY OTHER DAY.
- CONSULT A PHYSICIAN BEFORE USE.

Other Information

Store at 15-30°C (59-86°F)

INACTIVE INGREDIENT

INGREDIENTS

aqua (water), diglycerin, propanediol, butylene glycol, salicylic acid, allantoin, bisabolol, glycerin, angelica sinensis extract, avena sativa (oat) kernel extract, lecithin, ethylhexylglycerin, carbomer, acrylates/C10-30 alkyl acrylate , crosspolymer, aminomethyl propanol, phenoxyethanol, potassium sorbate